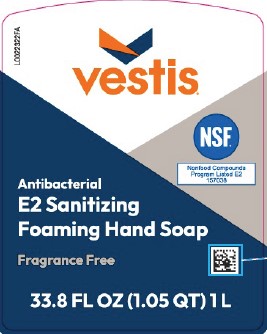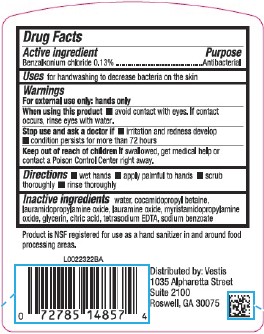 DRUG LABEL: Foaming Hand
NDC: 71897-224 | Form: SOAP
Manufacturer: Veritiv Operating Company
Category: otc | Type: HUMAN OTC DRUG LABEL
Date: 20260216

ACTIVE INGREDIENTS: BENZALKONIUM CHLORIDE 1.3 mg/1 mL
INACTIVE INGREDIENTS: LAURAMIDOPROPYLAMINE OXIDE; COCAMIDOPROPYL BETAINE; WATER; TETRASODIUM EDTA; CITRIC ACID; GLYCERIN; MYRISTAMIDOPROPYLAMINE OXIDE; LAURAMINE OXIDE; SODIUM BENZOATE

Vestis 224.000/224AA
Sanitizing Foaming Hand Soap

Active Ingredient

Benzalkonium chloride 0.13 %

Purpose

Antibacterial

Uses

for handwashing to decrease bacteria on the skin

Warnings

For external use only: hands only

When using this product

- avoid contact with eyes. If contact occurs, rinse eyes with water.

Stop use and ask a doctor if

- irritation and redness develop
- condition persists for more than 72 hours

Keep out of reach of children.

If swallowed, get medical help or contact a Poison Control Center right away.

Directions

- wet hands
- apply palmful to hands
- scrub thoroughly
- rinse thoroughly

Inactive ingredients

water, cocamidopropyl betaine, lauramidopropylamine oxide, lauramine oxide, myristamidopropylamine oxide, glycerin, citric acid, tetrasodium EDTA, sodium benzoate

Claim

Product is NSF registered for use as a hand sanitizer in and around fool processing areas.

Adverse Reaction

Distributed by: Vestis

1035 Alpharetta Street

Suite 2100

Roswell, GA 30075

Principal Display Panel

vestis®

NSF

Nonfood Compounds Program Listed E2 157038

Antibacterial

E2 Sanitizing

Foaming Hand Soap

Fragrance Free

33.8 FL OZ (1.05 QT) 1 L